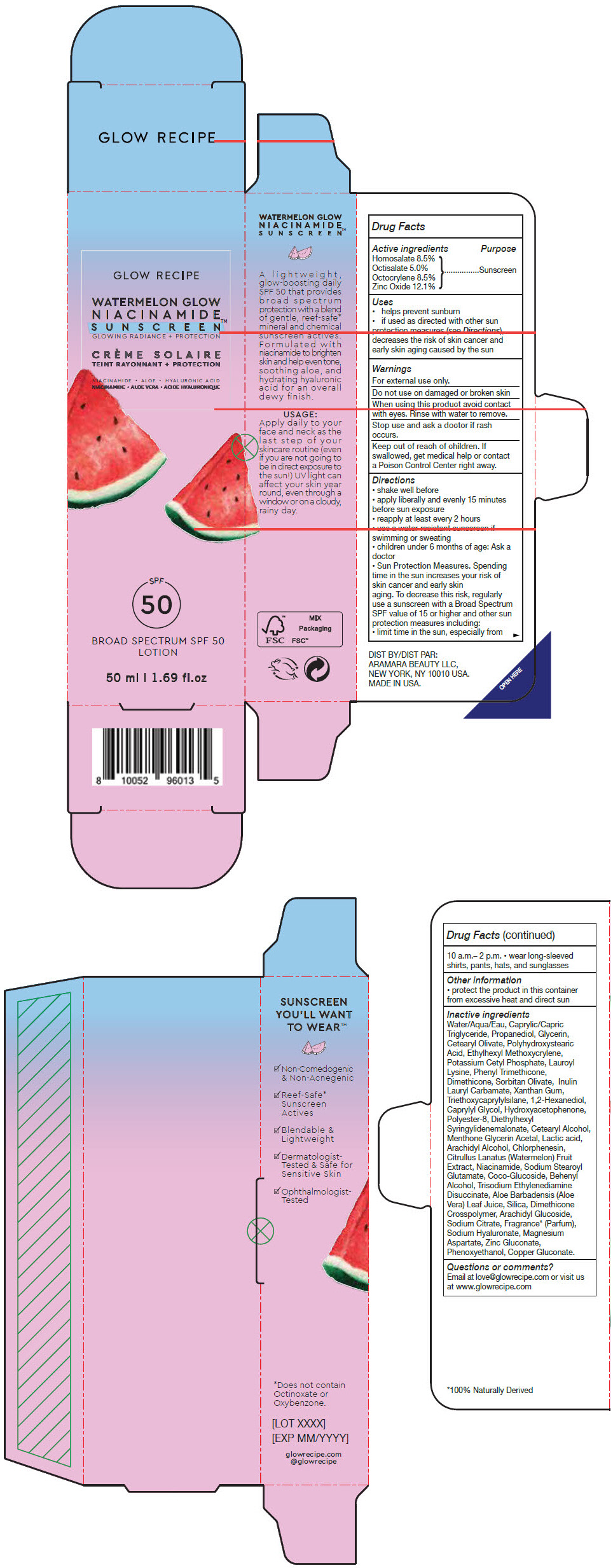 DRUG LABEL: WATERMELON GLOW NIACINAMIDE SUNSCREEN
NDC: 72156-002 | Form: LOTION
Manufacturer: Aramara Beauty
Category: otc | Type: HUMAN OTC DRUG LABEL
Date: 20231211

ACTIVE INGREDIENTS: HOMOSALATE 85 mg/1 mL; OCTISALATE 50 mg/1 mL; OCTOCRYLENE 85 mg/1 mL; ZINC OXIDE 121 mg/1 mL
INACTIVE INGREDIENTS: WATER; TRICAPRIN; PROPANEDIOL; GLYCERIN; CETEARYL OLIVATE; ETHYLHEXYL METHOXYCRYLENE; POTASSIUM CETYL PHOSPHATE; LAUROYL LYSINE; PHENYL TRIMETHICONE; DIMETHICONE; SORBITAN OLIVATE; XANTHAN GUM; TRIETHOXYCAPRYLYLSILANE; 1,2-HEXANEDIOL; CAPRYLYL GLYCOL; HYDROXYACETOPHENONE; POLYESTER-8 (1400 MW, CYANODIPHENYLPROPENOYL CAPPED); DIETHYLHEXYL SYRINGYLIDENEMALONATE; CETOSTEARYL ALCOHOL; MENTHONE 1,2-GLYCEROL KETAL, (+/-)-; LACTIC ACID, UNSPECIFIED FORM; ARACHIDYL ALCOHOL; CHLORPHENESIN; WATERMELON; NIACINAMIDE; SODIUM STEAROYL GLUTAMATE; COCO GLUCOSIDE; DOCOSANOL; TRISODIUM ETHYLENEDIAMINE DISUCCINATE; ALOE VERA LEAF; SILICON DIOXIDE; DIMETHICONE CROSSPOLYMER (450000 MPA.S AT 12% IN CYCLOPENTASILOXANE); ARACHIDYL GLUCOSIDE; SODIUM CITRATE, UNSPECIFIED FORM; HYALURONATE SODIUM; MAGNESIUM ASPARTATE; ZINC GLUCONATE; PHENOXYETHANOL; COPPER GLUCONATE

WATERMELON GLOW NIACINAMIDE SUNSCREEN™

Drug Facts

Active ingredients

Homosalate 8.5%
Octisalate 5.0%
Octocrylene 8.5%
Zinc Oxide 12.1%

Purpose

Sunscreen

Uses

- helps prevent sunburn
- if used as directed with other sun protection measures (see Directions), decreases the risk of skin cancer and early skin aging caused by the sun

Warnings

For external use only.

Do not useon damaged or broken skin

WHEN USING

When using this productavoid contact with eyes. Rinse with water to remove.

Stop use and ask a doctor ifrash occurs.

Keep out of reach of children.If swallowed, get medical help or contact a Poison Control Center right away.

Directions

- shake well before
- apply liberally and evenly 15 minutes before sun exposure
- reapply at least every 2 hours
- use a water-resistant sunscreen if swimming or sweating
- children under 6 months of age: Ask a doctor
- Sun Protection Measures.Spending time in the sun increases your risk of skin cancer and early skin aging. To decrease this risk, regularly use a sunscreen with a Broad Spectrum SPF value of 15 or higher and other sun protection measures including:
  - limit time in the sun, especially from 10 a.m.– 2 p.m.
  - wear long-sleeved shirts, pants, hats, and sunglasses

Other information

- protect the product in this container from excessive heat and direct sun

Inactive ingredients

Water/Aqua/Eau, Caprylic/Capric Triglyceride, Propanediol, Glycerin, Cetearyl Olivate, Polyhydroxystearic Acid, Ethylhexyl Methoxycrylene, Potassium Cetyl Phosphate, Lauroyl Lysine, Phenyl Trimethicone, Dimethicone, Sorbitan Olivate, Inulin Lauryl Carbamate, Xanthan Gum, Triethoxycaprylylsilane, 1,2-Hexanediol, Caprylyl Glycol, Hydroxyacetophenone, Polyester-8, Diethylhexyl Syringylidenemalonate, Cetearyl Alcohol, Menthone Glycerin Acetal, Lactic acid, Arachidyl Alcohol, Chlorphenesin, Citrullus Lanatus (Watermelon) Fruit Extract, Niacinamide, Sodium Stearoyl Glutamate, Coco-Glucoside, Behenyl Alcohol, Trisodium Ethylenediamine Disuccinate, Aloe Barbadensis (Aloe Vera) Leaf Juice, Silica, Dimethicone Crosspolymer, Arachidyl Glucoside, Sodium Citrate, Fragrance [100% Naturally Derived] (Parfum), Sodium Hyaluronate, Magnesium Aspartate, Zinc Gluconate, Phenoxyethanol, Copper Gluconate.

Questions or comments?

Email at love@glowrecipe.com or visit us at www.glowrecipe.com

DIST BY:
ARAMARA BEAUTY LLC,
NEW YORK, NY 10010 USA.

PRINCIPAL DISPLAY PANEL - 50 ml Tube Carton

GLOW RECIPE

WATERMELON GLOW
NIACINAMIDE
SUNSCREEN™
GLOWING RADIANCE + PROTECTION

NIACINAMIDE • ALOE • HYALURONIC ACID

SPF
50

BROAD SPECTRUM SPF 50
LOTION

50 ml | 1.69 fl.oz